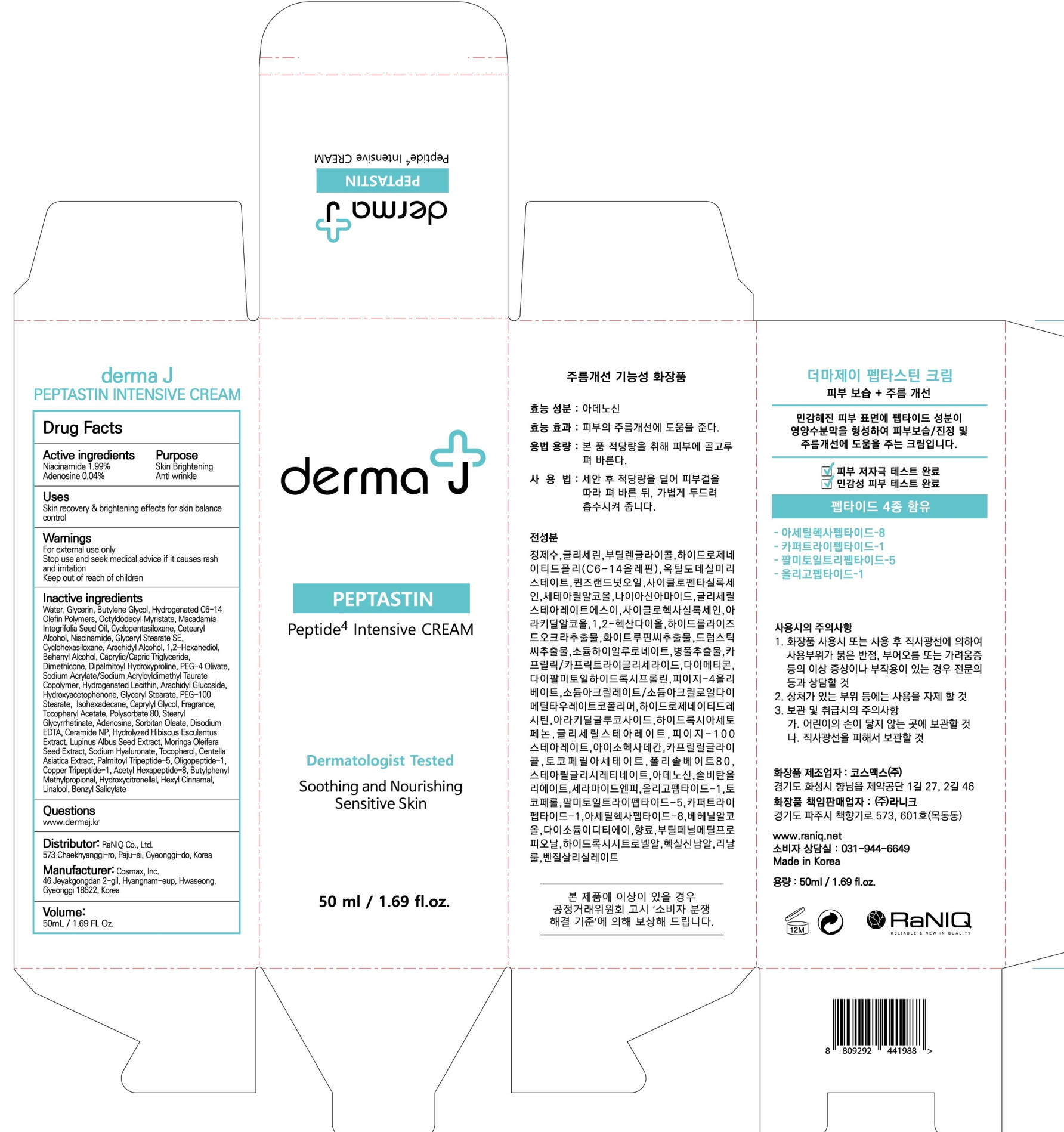 DRUG LABEL: derma J PEPTASTIN INTENSIVE
NDC: 73225-030 | Form: CREAM
Manufacturer: Raniq. Co., Ltd
Category: otc | Type: HUMAN OTC DRUG LABEL
Date: 20200310

ACTIVE INGREDIENTS: Niacinamide 0.99 g/50 mL; Adenosine 0.02 g/50 mL
INACTIVE INGREDIENTS: Water; Glycerin

ACTIVE INGREDIENT

Active ingredients: Niacinamide 1.99%, Adenosine 0.04%

INACTIVE INGREDIENT

Inactive ingredients:

Water, Glycerin, Butylene Glycol, Hydrogenated C6-14 Olefin Polymers, Octyldodecyl Myristate, Macadamia Integrifolia Seed Oil, Cyclopentasiloxane, Cetearyl Alcohol, Glyceryl Stearate SE, Cyclohexasiloxane, Arachidyl Alcohol, 1,2-Hexanediol, Behenyl Alcohol, Caprylic/Capric Triglyceride, Dimethicone, Dipalmitoyl Hydroxyproline, PEG-4 Olivate, Sodium Acrylate/Sodium Acryloyldimethyl Taurate Copolymer, Hydrogenated Lecithin, Arachidyl Glucoside, Hydroxyacetophenone, Glyceryl Stearate, Isohexadecane, Caprylyl Glycol, Fragrance, Tocopheryl Acetate, Polysorbate 80, Stearyl Glycyrrhetinate, Sorbitan Oleate, Disodium EDTA, Ceramide NP, Hydrolyzed Hibiscus Esculentus Extract, Lupinus Albus Seed Extract, Moringa Oleifera Seed Extract, Sodium Hyaluronate, Tocopherol, Centella Asiatica Extract, Palmitoyl Tripeptide-5, Oligopeptide-1, Copper Tripeptide-1, Acetyl Hexapeptide-8, Butylphenyl Methylpropional, Hydroxycitronellal, Hexyl Cinnamal, Linalool, Benzyl Salicylate

PURPOSE

Purpose: Skin Brightening, Anti wrinkle

WARNINGS

For external use only
Stop use and seek medical advice if it causes rash and irritation
Keep out of reach of children

KEEP OUT OF REACH OF CHILDREN

QUESTIONS

www.dermaj.kr

Uses

Skin recovery & brightening effects for skin balance control

Directions

Apply an adequate amount on your skin after face wash for your daily care